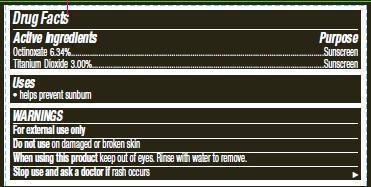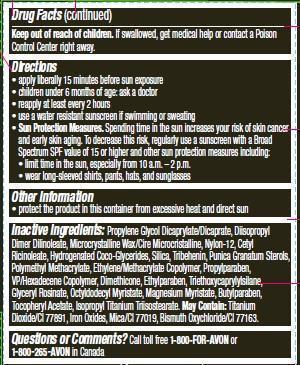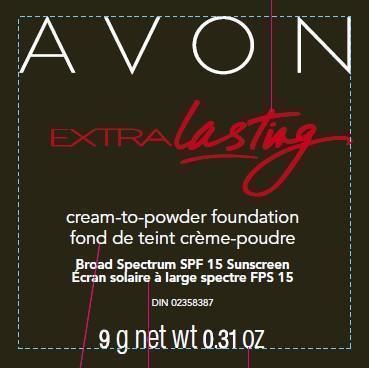 DRUG LABEL: Extralasting
NDC: 10096-0231 | Form: CREAM
Manufacturer: New Avon LLC
Category: otc | Type: HUMAN OTC DRUG LABEL
Date: 20160217

ACTIVE INGREDIENTS: OCTINOXATE 63.4 mg/1 g; TITANIUM DIOXIDE 30 mg/1 g

Active ingredients

Octinoxate 6.34%...................................

Titanium Dioxide 3.00%............................

Purpose
...................................Sunscreen
...................................Sunscreen

Uses
• helps prevent sunburn

WARNINGS
For external use only

Do not use on damaged or broken skin

When using this product keep out of eyes. Rinse with water to remove.

Stop use and ask a doctor if rash occurs

Keep out of reach of children. If swallowed, get medical help or contact a Poison Control Center right away.

Directions
• apply liberally 15 minutes before sun exposure
• children under 6 months of age: ask a doctor
• reapply at least every 2 hours
• use a water resistant sunscreen if swimming or sweating
• Sun Protection Measures. Spending time in the sun increases your risk of skin cancer and early skin aging. To decrease this risk, regularly use a sunscreen with a Broad Spectrum SPF value of 15 or higher and other sun protection measures including:

• limit time in the sun, especially from 10 a.m. – 2 p.m.

• wear long-sleeved shirts, pants, hats, and sunglasses

Other information
• protect the product in this container from excessive heat and direct sun

INACTIVE INGREDIENT

Inactive ingredients: Propylene Glycol Dicaprylate/Dicaprate, Diisopropyl Dimer Dilinoleate, Microcrystalline Wax/Cire Microcristalline, Nylon-12, Cetyl Ricinoleate, Hydrogenated Coco-Glycerides, Silica, Tribehenin, Punica Granatum Sterols, Polymethyl Methacrylate, Ethylene/Methacrylate Copolymer, Propylparaben, VP/Hexadecene Copolymer, Dimethicone, Ethylparaben, Triethoxycaprylylsilane, Glyceryl Rosinate, Octyldodecyl Myristate, Magnesium Myristate, Butylparaben, Tocopheryl Acetate, Isopropyl Titanium Triisostearate. May Contain: Titanium Dioxide/CI 77891, Iron Oxides, Mica/CI 77019, Bismuth Oxychloride/CI 77163.

Questions or Comments? Call toll free 1-800-FOR-AVON or 1-800-265-AVON in Canada